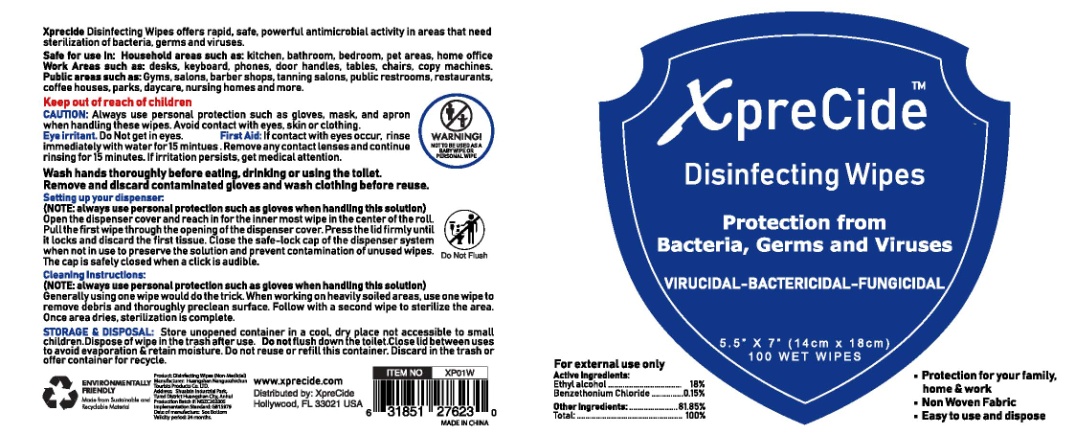 DRUG LABEL: WET WIPES
NDC: 78736-002 | Form: SWAB
Manufacturer: HUANGSHAN NANGUOZHICHUN TOURISTS PRODUCTS CO., LTD.
Category: otc | Type: HUMAN OTC DRUG LABEL
Date: 20200609

ACTIVE INGREDIENTS: ALCOHOL 18 g/100 g
INACTIVE INGREDIENTS: GLYCERIN 0.1 g/100 g; PHENOXYETHANOL 0.5 g/100 g; WATER; BENZALKONIUM CHLORIDE; ETHYLHEXYLGLYCERIN 0.1 g/100 g; GERANIAL PROPYLENE GLYCOL ACETAL

WET WIPES

Active Ingredient(s)

Alcohol 18% v/v. Purpose: Antiseptic

Purpose

Antiseptic

Use

Decreases bacteria on skin. Recommended for repeated use

Warnings

For external use only.Do not use over large areas of the body if you are allergic to any of the ingredients when using this product,avoid contact with eyes and face.If contact occurs,flush thoroughly with water.Stop use and ask a doctor if irritation or rash develops and continues for more than 72 hours.

Do not use

- in children less than 2 months of age
- on open skin wounds

Stop use and ask a doctor if irritation or rash occurs. These may be signs of a serious condition.

Keep out of reach of children. If swallowed, get medical help or contact a Poison Control Center right away.

Directions

For adults and children of 2 years and over.children under 2 years ask a doctor before use allow to dry without wiping

Inactive ingredients

Phenoxyethanol，Ethylhexylglycerin，Benzalkonium Chloride，DDAC，Propylene Glycol，Glycerin，Purified Water

Package Label - Principal Display Panel

100 PCS IN 1 PAIL NDC: 78736-002-01